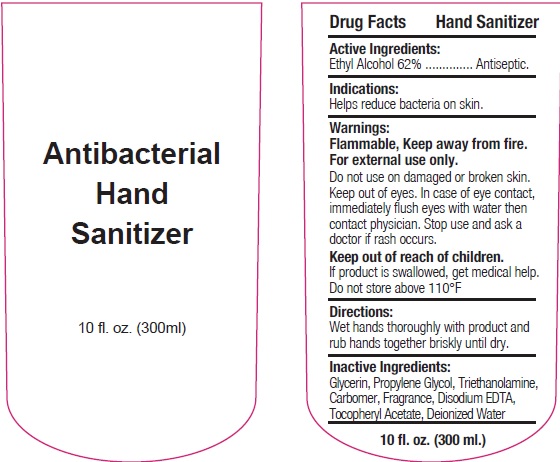 DRUG LABEL: HAND SANITIZER
NDC: 75613-009 | Form: GEL
Manufacturer: Ningbo Lanzi Cosmetic Technology Co., Ltd
Category: otc | Type: HUMAN OTC DRUG LABEL
Date: 20200809

ACTIVE INGREDIENTS: ALCOHOL 62 mL/100 mL
INACTIVE INGREDIENTS: WATER; PROPYLENE GLYCOL; EDETATE DISODIUM; TROLAMINE; .ALPHA.-TOCOPHEROL ACETATE, D-; GLYCERIN

HAND SANITIZER

Active ingredient

Ethyl Alcohol 62%

Purpose

Antiseptic

Use

Helps reduce bacteria on skin.

Warnings

For external use only

Flammable. Keep away from fire.

When using this product

Do not use on damaged or broken skin. keep out of eyes. In case of eye contact, immediately flush eyes with water then contact physician.

Stop use and ask a doctor if rah occurs.

Other Information:

- Do not store above 110℉

Keep out of reach of children.

If swallowed, get medical help or contact a Poison Control Center right away.

Directions

- Wet hands thoroughly with product and rub hands together briskly until dry.

Inactive ingredients

Glycerin, Propylene Glycol, Triethanolamine, Carbomer, Fragrance, Disodium edta, Tocopheryl acetate, Deionized Water